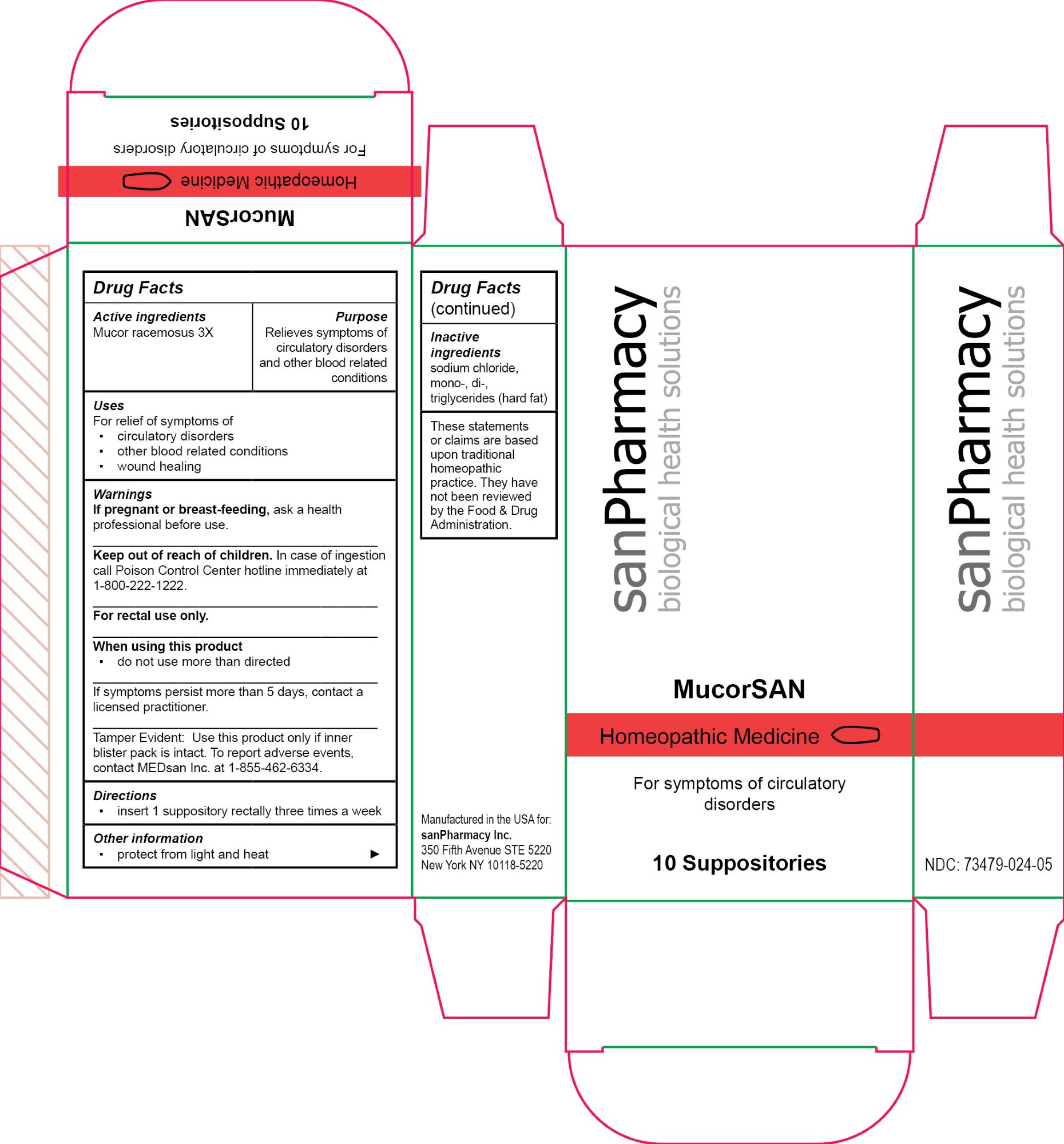 DRUG LABEL: MucorSAN
NDC: 73479-024 | Form: SUPPOSITORY
Manufacturer: sanPharmacy Inc.
Category: homeopathic | Type: HUMAN OTC DRUG LABEL
Date: 20240429

ACTIVE INGREDIENTS: MUCOR RACEMOSUS 3 [hp_X]/1 1
INACTIVE INGREDIENTS: HARD FAT; SODIUM CHLORIDE

MucorSAN Suppositories

Indications

For symptoms of circulatory disorders

Purpose

Relieves symptoms of circulatory disorders and other blood related conditions

Dosage

insert 1 suppository rectally three times a week

ACTIVE INGREDIENT

Mucor racemosus 3X

INACTIVE INGREDIENT

sodium chloride, mono-, di-, triglycerides (hard fat)

WARNINGS

If pregnant or breast-feeding, ask a health professional before use.
______________________________
Keep out of reach of children. In case of ingestion call Poison Control Center hotline immediately at 1-800-222-1222.
______________________________
For rectal use only.
______________________________
When using this product
▪ do not use more than directed
______________________________
If symptoms persist more than 5 days, contact a licensed practitioner.
______________________________
Tamper Evident: Use this product only if inner blister pack is intact. To report adverse events, contact MEDsan Inc. at 1-855-462-6334.

Keep out of reach of children. In case of ingestion call Poison Control Center hotline immediately at 1-800-222-1222

Manufactured in the USA for:
sanPharmacy Inc.
350 Fifth Avenue STE 5220
New York NY 10118-5220

Liability statement

These statements or claims are based upon traditional homeopathic practice. They have not been reviewed by the Food & Drug Administration

Storage

protect from light and heat

PACKAGE LABEL

MucorSAN

Homeopathic Medicine

For symptoms of circulatory disorders

10 Suppositories

sanPharmacy

biological health solutions